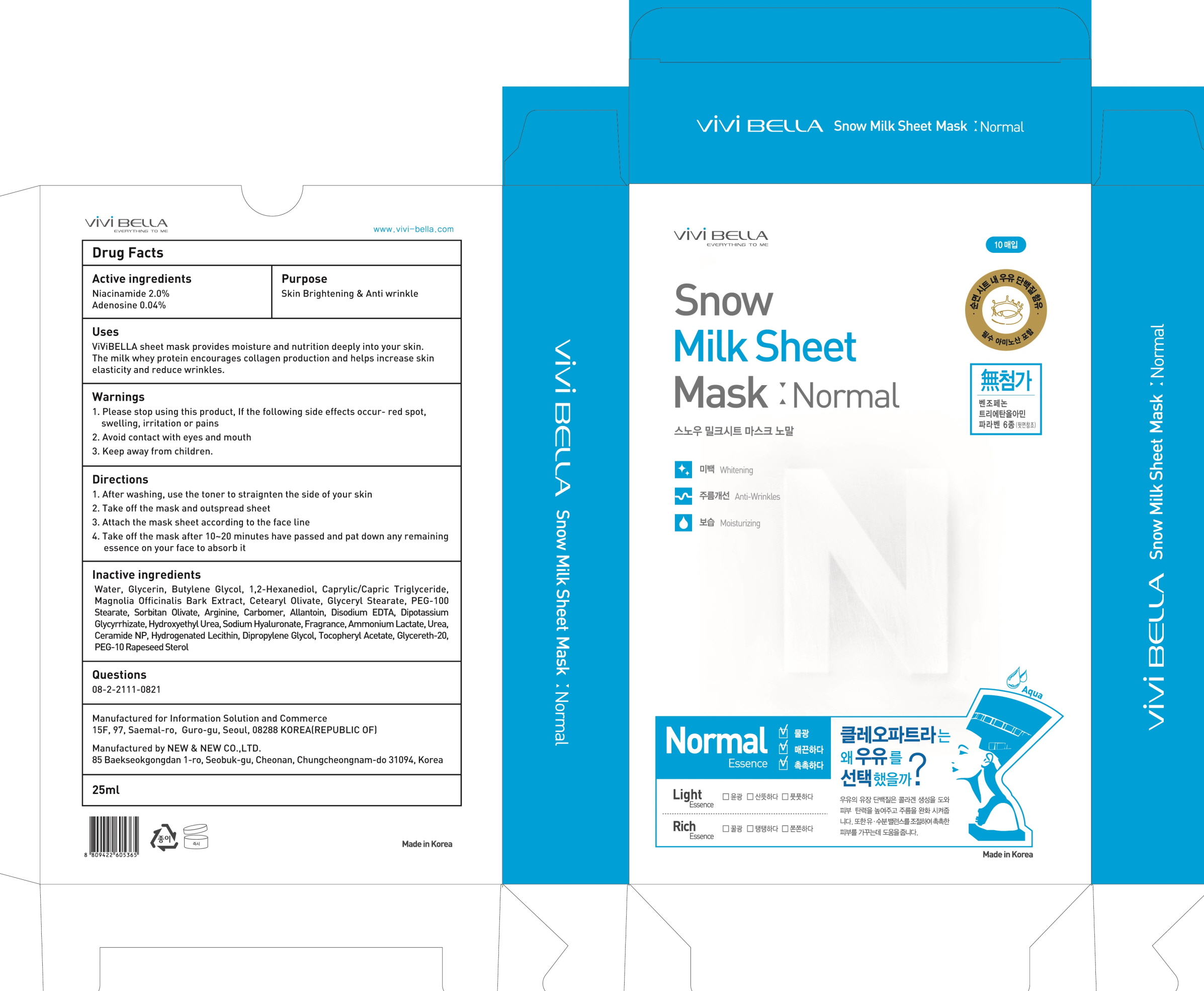 DRUG LABEL: Snow Milk Sheet Mask Normal
NDC: 71947-010 | Form: PATCH
Manufacturer: Information Solution & Commerce Co., Ltd.
Category: otc | Type: HUMAN OTC DRUG LABEL
Date: 20180104

ACTIVE INGREDIENTS: Niacinamide 0.50 g/25 mL; Adenosine 0.01 g/25 mL
INACTIVE INGREDIENTS: Water; Glycerin

ACTIVE INGREDIENT

Active ingredients: Niacinamide 2.0%, Adenosine 0.04%

INACTIVE INGREDIENT

Inactive ingredients: Water, Glycerin, Butylene Glycol, 1,2-Hexanediol, Caprylic/Capric Triglyceride, Magnolia Officinalis Bark Extract, Cetearyl Olivate, Glyceryl Stearate, PEG-100 Stearate, Sorbitan Olivate, Arginine, Carbomer, Allantoin, Disodium EDTA, Dipotassium Glycyrrhizate, Hydroxyethyl Urea, Sodium Hyaluronate, Fragrance, Ammonium Lactate, Urea, Ceramide NP, Hydrogenated Lecithin, Dipropylene Glycol, Tocopheryl Acetate, Glycereth-20, PEG-10 Rapeseed Sterol

PURPOSE

Purpose: Skin Brightening & Anti wrinkle

WARNINGS

Warnings: 1. Please stop using this product, If the following side effects occur- red spot, swelling, irritation or pains 2. Avoid contact with eyes and mouth 3. Keep away from children.

KEEP OUT OF REACH OF CHILDREN

Keep away from children

Uses

Uses: ViViBELLA sheet mask provides moisture and nutrition deeply into your skin. The milk whey protein encourages collagen production and helps increase skin elasticity and reduce wrinkles.

Directions

1. After washing, use the toner to straignten the side of your skin

2. Take off the mask and outspread sheet

3. Attach the mask sheet according to the face line

4. Take off the mask after 10~20 minutes have passed and pat down any remaining essence on your face to absorb it